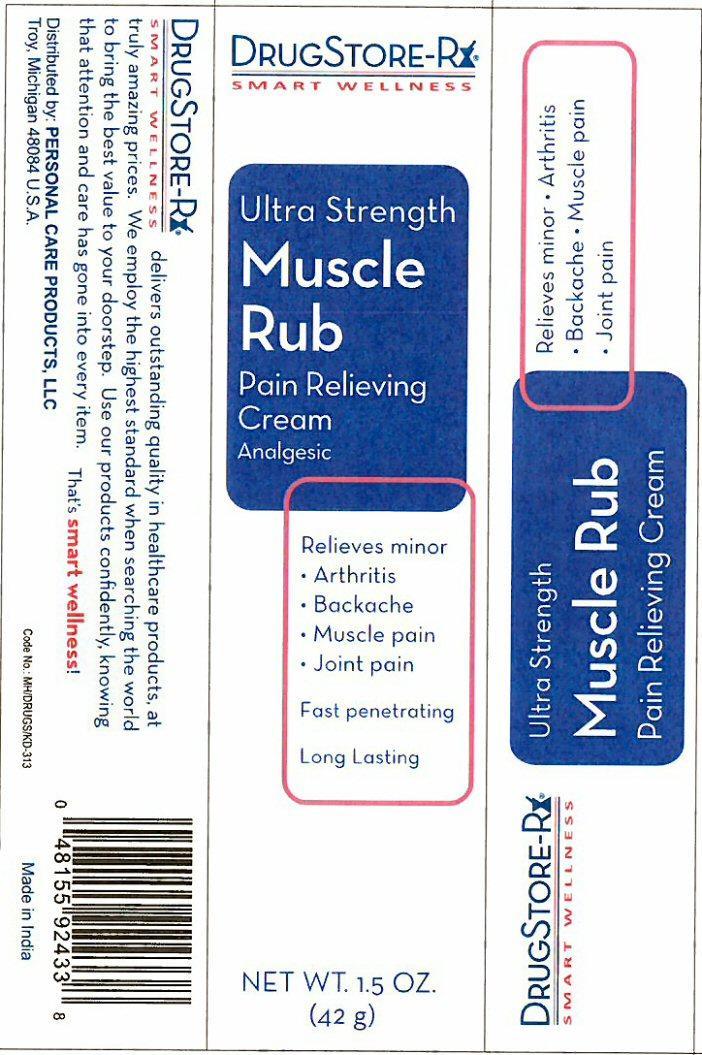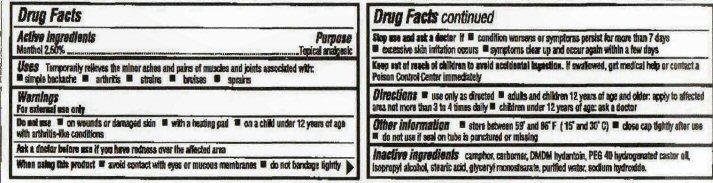 DRUG LABEL: Muscle Rub
NDC: 29500-2433 | Form: CREAM
Manufacturer: Personal Care Products, Inc.
Category: otc | Type: HUMAN OTC DRUG LABEL
Date: 20130710

ACTIVE INGREDIENTS: MENTHOL 1.05 g/42 g
INACTIVE INGREDIENTS: CAMPHOR (NATURAL); CARBOMER HOMOPOLYMER TYPE C (ALLYL PENTAERYTHRITOL CROSSLINKED); DMDM HYDANTOIN; POLYOXYL 40 HYDROGENATED CASTOR OIL; ISOPROPYL ALCOHOL; STEARIC ACID; WATER; SODIUM HYDROXIDE; GLYCERYL MONOSTEARATE

Active Ingredient

Drug Facts

Menthol 2.5%

Purpose

Topical analgesic

Keep out of reach of children to avoid accidental ingestion. If swallowed, get medical help or contact a Poison Control Center immediately.

Uses

Temporarily relieves the minor aches and pains of muscles and joints associated with:

- simple backache
- arthritis
- strains
- bruises
- sprains

Warnings

For external use only.
Do not use on

- on wounds or damaged skin

- with a heating pad

- on a child under 12 years of age with arthritis-like conditions

Ask a doctor before use if you have redness over the affected area.
When using this product

- avoid contact with eyes or mucus membranes
- do not bandage tightly

Stop use and ask a doctor if

- condition worsens or symptoms persist for more than 7 days
- excessive skin irritation occurs
- symptoms clear up and occur again within a few days

Directions

- use only as directed
- adults and children 12 years of age and older: apply to affected area not more than 3 to 4 times daily
- children under 12 years of age: ask a doctor

Other information

- store between 59° and 86° F (15° and 30° C)
- close cap tightly after use
- do not use if seal on tube is punctured or missing

Inactive ingredients

camphor, carbomer, DMDM hydantoin,PEG-40 hydrogenated castor oil, isopropyl alcohol, stearic acid, glyceryl monostearate, purified water, sodium hydroxide.

Product Label

DRUGSTORE-Rx
SMART WELLNESS
Ultra Strength
Muscle Rub
Pain Relieving Cream Analgesic
Relieves minor

- Arthritis
- Backache
- Muscle pain
- Joint pain

Fast penetrating
Long lasting
NET WT. 1.5 OZ. (42 g)
DRUGSTORE-Rx
SMART WELLNESS delivers outstanding quality in healthcare products, at truly amazing prices. We employ the highest standard when searching the world to bring the best value to your doorstep. Use our products confidently, knowing that attention and care has gone into every item. That's smart wellness!
Distributed by: PERSONAL CARE PRODUCTS, LLC
Troy, Michigan 48084 U.S.A.
Code No. MH/DRUGS/KD-313 Made in India